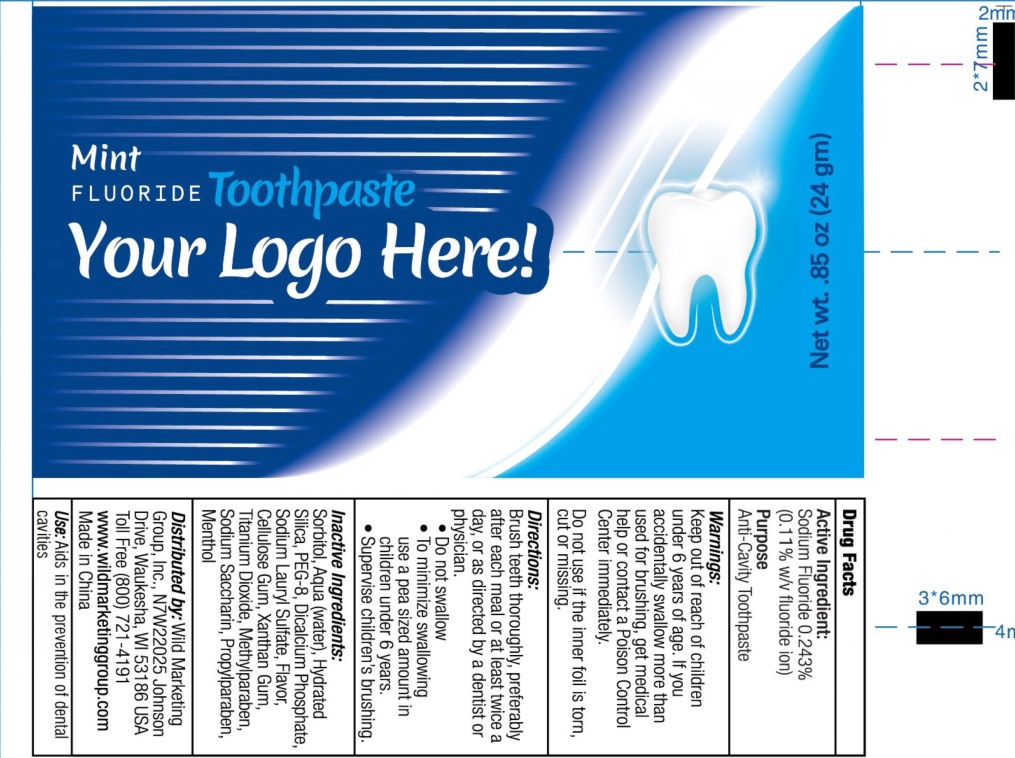 DRUG LABEL: Mint Fluoride Tooth
NDC: 70766-011 | Form: PASTE, DENTIFRICE
Manufacturer: Yangzhou SION Commodity Co.,Ltd
Category: otc | Type: HUMAN OTC DRUG LABEL
Date: 20231208

ACTIVE INGREDIENTS: SODIUM FLUORIDE 0.11 g/100 g
INACTIVE INGREDIENTS: WATER; SORBITOL; XANTHAN GUM; HYDRATED SILICA; SODIUM LAURYL SULFATE; MENTHOL; CALCIUM PHOSPHATE, DIBASIC, ANHYDROUS; METHYLPARABEN; PROPYLPARABEN; TITANIUM DIOXIDE; SACCHARIN SODIUM

70766-011 Mint Fluorine Toothpaste

Active ingredients

SODIUM FLUORIDE 0.243%(0.11 w/v Fluoride ion)

Purpose

Anti-cavity toothpaste

Uses

aids in the prevention of cavities.

Warnings

Keep out of the reach of children under 6 years of age. If accidently swallow more than used for brushing,get medical help or contact a Poison Control Center immediately.

Do not use if the inner foil is torn, cut, or missing

Keep out of reach of children.

Directions

Brush teeth thoroughly, preferrably after each meal or at least twice a day, or as directed by a dentist or a physician

Do not swallow

To minimize wallowing, use a pea sizes amount in children under 6 years

Supervise children's brushing

INACTIVE INGREDIENT

Sorbitol, Hydrated silica,Water, PEG-8, Sodium lauryl sulfate, Cellulose gum, Xanthan gum, flavor, Menthol, Dicalcium Phosphate, Methylparaben, Propylparaben, Titanium Dioxide, sodium sacharine